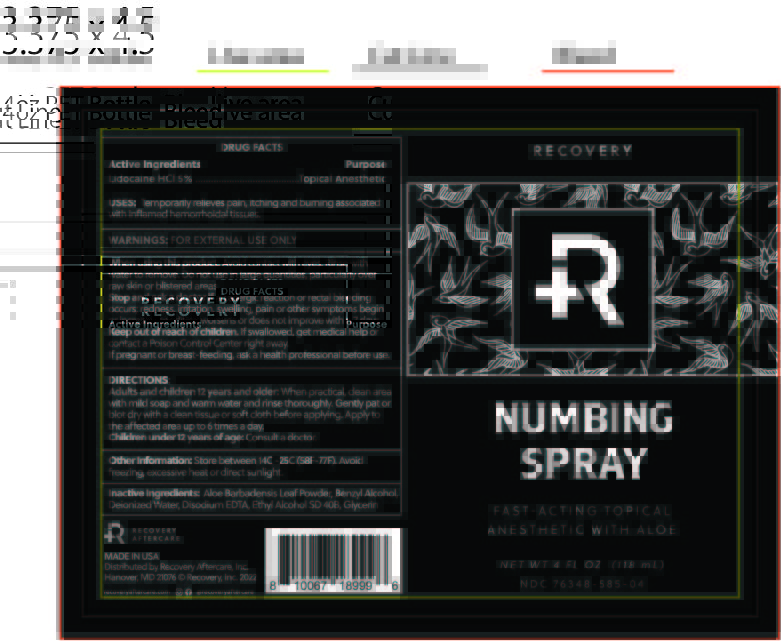 DRUG LABEL: RECOVERY Numbing
NDC: 76348-980 | Form: SPRAY
Manufacturer: Renu Laboratories, LLC
Category: otc | Type: HUMAN OTC DRUG LABEL
Date: 20250606

ACTIVE INGREDIENTS: LIDOCAINE HYDROCHLORIDE 5.9 g/118 mL
INACTIVE INGREDIENTS: BENZYL ALCOHOL; ALCOHOL; GLYCERIN; ALOE VERA LEAF; WATER; EDETATE DISODIUM ANHYDROUS

RECOVERY NUMBING SPRAY

Active Ingredients

Lidocaine HCl 5 %

Purpose

Topical Anesthetic

INDICATIONS AND USAGE

USES: Temporarily relieves pain, itching and burning associated with inflamed hemorrhoidal tissues.

WARNINGS: FOR EXTERNAL USE ONLY

STOP USE

Stop and ask a doctor if an allergic reaction or rectal bleeding occurs; redness, irritation, swelling, pain or other symptoms begin or increase; condition worsens or does not improve within 7 days.

Keep out of reach of children. If swallowed, get medical help or contact a Poison Control Center right away. If pregnant or breast-feeding, ask a health professional before use.

PREGNANCY OR BREAST FEEDING

If pregnant or breast-feeding, ask a health professional before use.

DIRECTIONS:

Adults and children 12 years and older: When practical, clean area with mild soap and warm water and rinse thoroughly. Gently pat or blot dry with a clean tissue or soft cloth before applying. Apply to the affected area up to 6 times a day.

Children under 12 years of age: Consult a doctor.

Other information: Store between 14C - 25C (58F - 77F). Avoid freezing, excessive heat or direct sunlight.

INACTIVE INGREDIENT

Inactive Ingredients: Aloe Barbadensis Leaf Powder, Benzyl Alcohol, Deionized Water, Disodium EDTA, Ethyl Alcohol SD 40B, Glycerin

STATEMENT OF IDENTITY

RECOVERY

NUMBING SPRAY

FAST-ACTING TOPICAL

ANESTHETIC WITH ALOE

NET WT 4 FL OZ (118 mL)

NDC 76348-585-04

When using this product avoid contact with eyes

Rinse with water to remove

Do not use in large quantities particularl over raw skin or blistered areas

PRODUCT LABEL